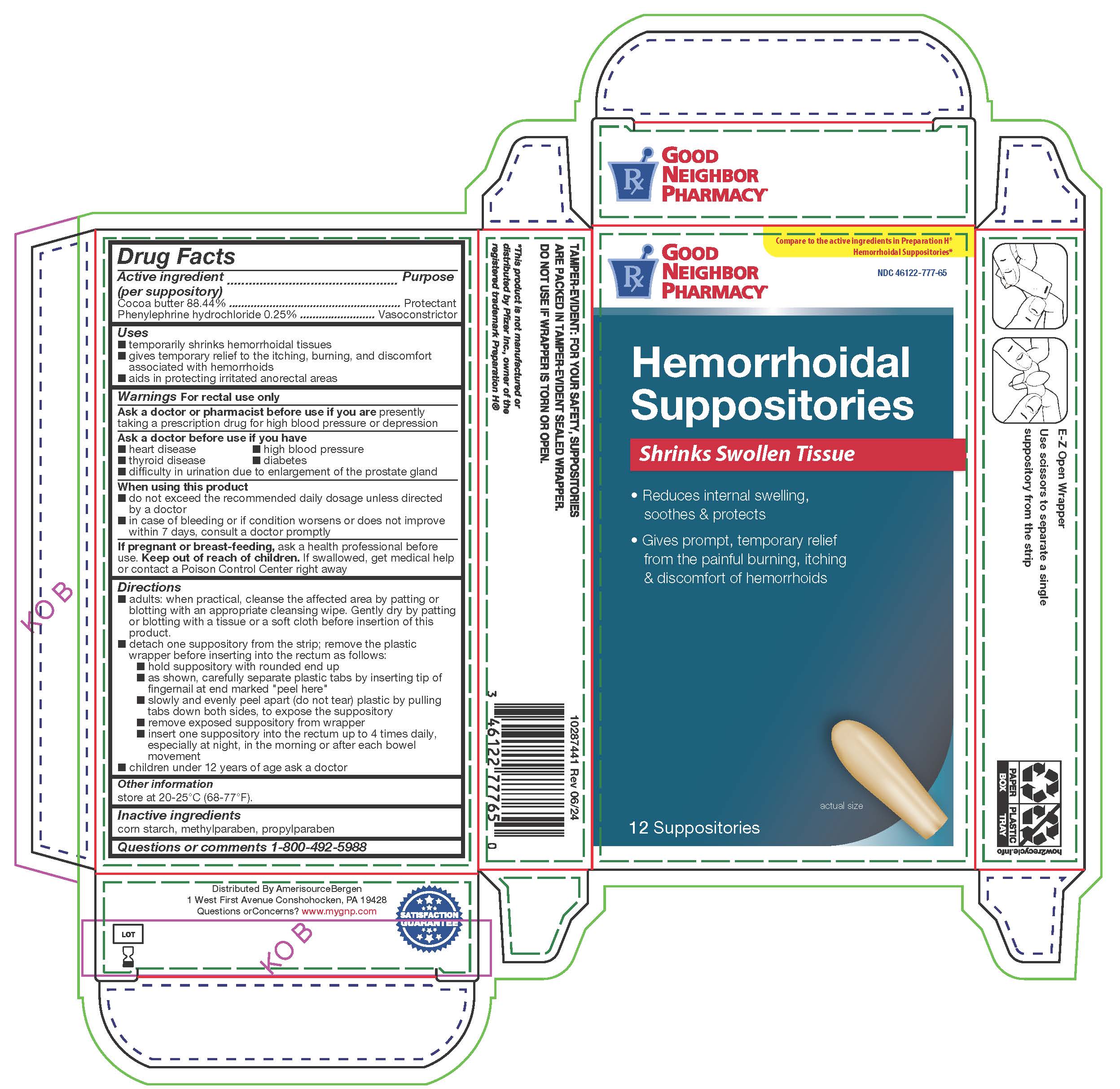 DRUG LABEL: Hemorrhoidal
NDC: 46122-777 | Form: SUPPOSITORY
Manufacturer: Amerisourcebergen Drug Corporation
Category: otc | Type: HUMAN OTC DRUG LABEL
Date: 20251024

ACTIVE INGREDIENTS: COCOA BUTTER 2.39 g/1 1; PHENYLEPHRINE HYDROCHLORIDE 6.75 mg/1 1
INACTIVE INGREDIENTS: STARCH, CORN; METHYLPARABEN; PROPYLPARABEN

GNP Hemmorrhoidal Suppositories

Active Ingredients (per suppository)

Cocoa butter 88.44%

Phenylephrine hydrochloride 0.25%

Purpose

Protectant

Vasoconstrictor

Uses

- temporarily shrinks hemorrhoidal tissue
- gives temporary relief to the itching, burning and discomfort associated with hemorrhoids
- aids in protecting irritated anorectal areas

Warnings

For rectal use only

Ask a doctor or pharmacist before use if you are

presently taking a prescription drug for high blood pressure or depression

Ask a doctor before use if you have

- heart disease
- thyroid disease
- difficulty in urination due to enlargement of the prostate gland
- high blood pressure
- diabetes

When using this product

- do not exceed the recommended daily dosage unless directed by a doctor
- in case of bleeding or if condition worsens or does not improve within 7 days, consult a doctor promptly

If pregnant or breast-feeding,

ask a health professional before use.

Keep out of reach of children.

If swallowed, get medical help or contact a Poison Control Center right away

Directions

- Adults: when practical, cleanse the affected area by patting or blotting with an appropriate cleansing wipe. Gently dry by patting or blotting with a tissue or soft cloth before insertion of this product.
- Detach one suppository from the strip; remove plastic wrapper before inserting into the rectum as follows:

- hold suppository with rounded end up
- as shown, carefully separate plastic tabs by inserting tip of finger nail at end marked "peep here"
- slowly and evenly peel apart (do not tear) plastic by pulling tabs down both sides, to expose the suppository
- remove exposed suppository from wrapper
- insert on suppository into the rectum up to 4 times daily, especially at night, in the morning or after each bowl movement

- children under 12 years of age ask a doctor

Other information

store at 20-25°C (68-77ºF)

Inactive ingredients

corn starch, methylparaben, propylparaben

Questions or comments?

1-800-492-5988

PACKAGE LABEL

The product package shown below represents a sample of that currently in use. Additional packaging may also be available.

GNP Hemorrhoidal Suppositories 12ct

Distributed Amerisource Bergen

1 West First Avenue

Conshohocken, PA 19428

785PVHemSupp.jpg